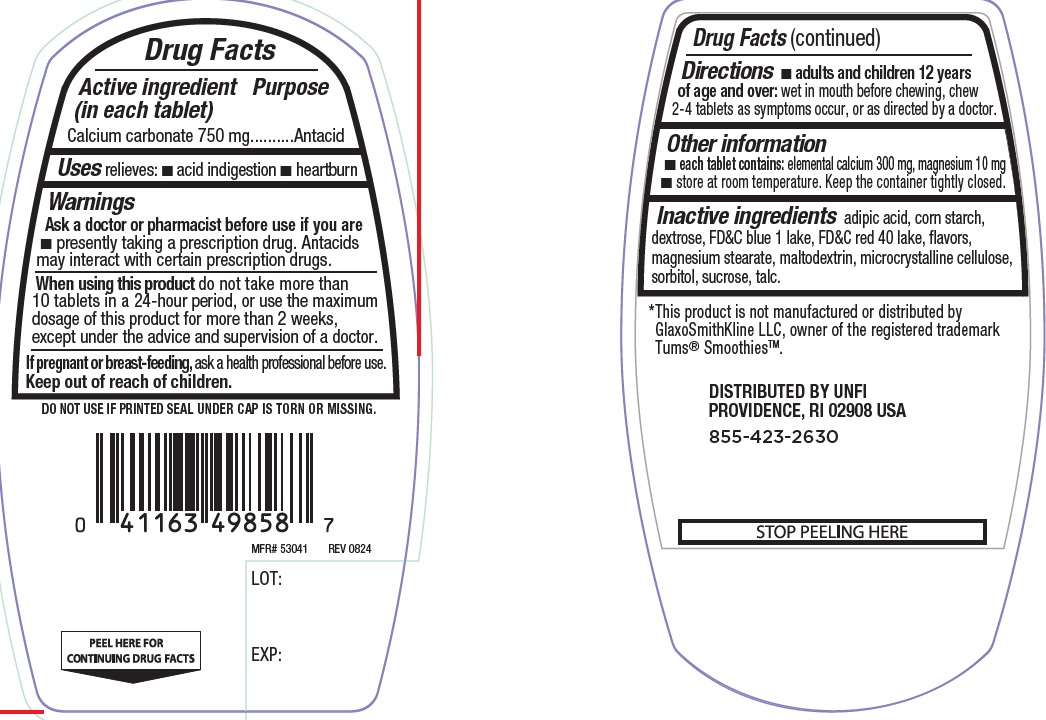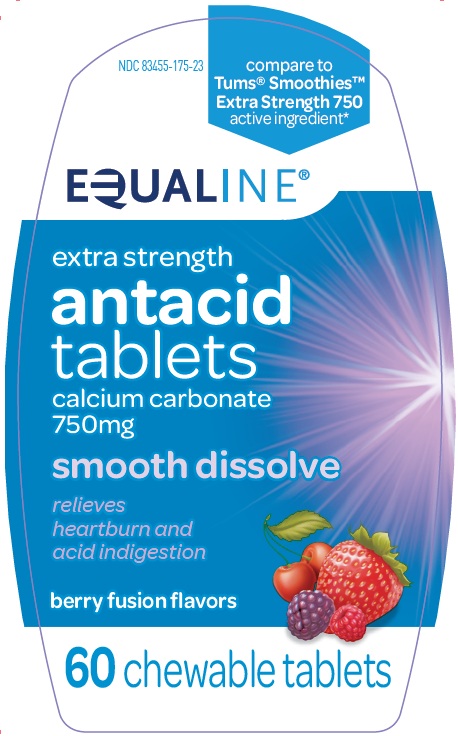 DRUG LABEL: Extra Strength Smooth Antacid
NDC: 83455-175 | Form: TABLET, CHEWABLE
Manufacturer: UNITED NATURAL FOODS, INC. DBA UNFI
Category: otc | Type: Human OTC Drug Label
Date: 20250207

ACTIVE INGREDIENTS: CALCIUM CARBONATE 750 mg/1 1
INACTIVE INGREDIENTS: ADIPIC ACID; STARCH, CORN; DEXTROSE, UNSPECIFIED FORM; FD&C BLUE NO. 1 ALUMINUM LAKE; FD&C RED NO. 40 ALUMINUM LAKE; MAGNESIUM STEARATE; MALTODEXTRIN; SUCROSE; TALC; SORBITOL; MICROCRYSTALLINE CELLULOSE

Extra Strength Smooth Berry Fusion Antacid

ACTIVE INGREDIENT (in each tablet)

Calcium carbonate 750 mg

PURPOSE

Antacid

USE(S)

relieves:

- acid indigestion
- heartburn

WARNINGS

.

ASK A DOCTOR OR PHARMACIST BEFORE USE IF YOU ARE

- presently taking a prescription drug. Antacids may interact with certain prescription drugs.

WHEN USING THIS PRODUCT

do not take more than 10 tablets in a 24-hour period, or use the maximum dosage of this product for more than 2 weeks, except under the advice and supervision of a doctor.

IF PREGNANT OR BREAST FEEDING,

ask a health professional before use.

KEEP OUT OF REACH OF CHILDREN

.

DIRECTIONS

- adults and children 12 years of age and over: wet in mouth before chewing, chew 2-4 tablets as symptoms occur, or as directed by a doctor.

OTHER INFORMATION

- each tablet contains: elemental calcium 300 mg, magnesium 10 mg
- store at room temperature. keep the container tightly closed.

INACTIVE INGREDIENTS

adipic acid, corn starch, dextrose, FD&C blue 1 lake, FD&C red 40 lake, flavors, magnesium stearate, maltodextrin, microcrystalline cellulose, sorbitol, sucrose, talc.

PRINCIPAL DISPLAY PANEL

NDC 83455-175-23

Compare to Tums® Smoothies™ Extra Strength 750 active ingredient*

EQUALINE®

extra strength
antacid tablets

Calcium Carbonate 750 mg

smooth dissolve

relieves

heartburn and

acid indigestion

berry fusion flavor

60 CHEWABLE TABLETS